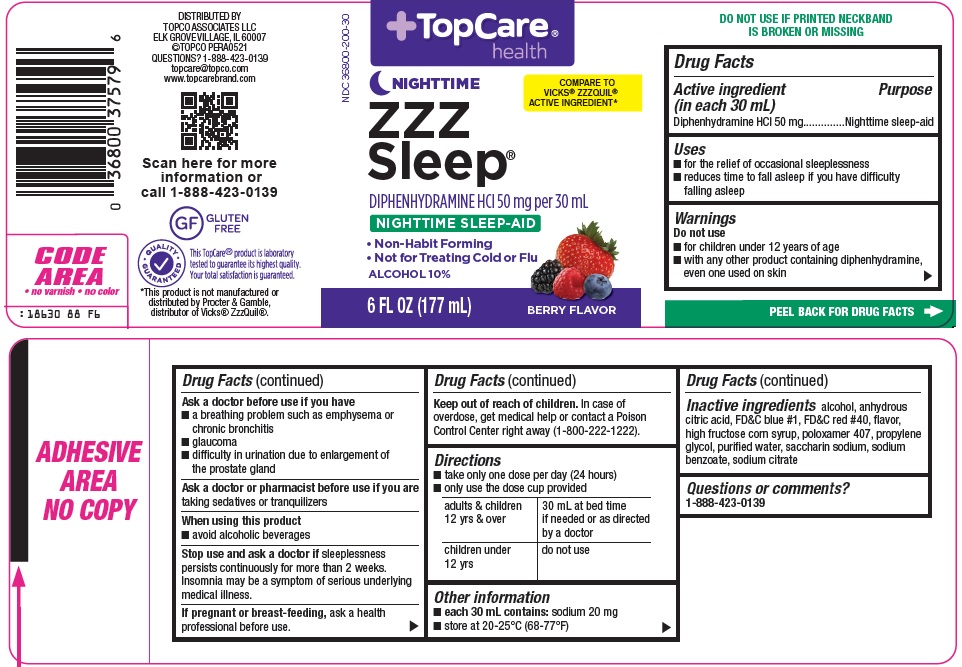 DRUG LABEL: Topcare ZZZ Sleep
NDC: 36800-200 | Form: SOLUTION
Manufacturer: Topco Associates LLC
Category: otc | Type: HUMAN OTC DRUG LABEL
Date: 20251211

ACTIVE INGREDIENTS: DIPHENHYDRAMINE HYDROCHLORIDE 50 mg/30 mL
INACTIVE INGREDIENTS: ALCOHOL; ANHYDROUS CITRIC ACID; FD&C BLUE NO. 1; FD&C RED NO. 40; HIGH FRUCTOSE CORN SYRUP; POLOXAMER 407; PROPYLENE GLYCOL; WATER; SACCHARIN SODIUM; SODIUM BENZOATE; SODIUM CITRATE, UNSPECIFIED FORM

Topco Associates LLC. ZZZ Sleep® Drug Facts

Active ingredient (in each 30 mL)

Diphenhydramine HCl 50 mg

Purpose

Nighttime sleep-aid

Uses

- for the relief of occasional sleeplessness
- reduces time to fall asleep if you have difficulty falling asleep

Warnings

Do not use

- for children under 12 years of age
- with any other product containing diphenhydramine, even one used on skin

Ask a doctor before use if you have

- a breathing problem such as emphysema or chronic bronchitis
- glaucoma
- difficulty in urination due to enlargement of the prostate gland

Ask a doctor or pharmacist before use if you are

taking sedatives or tranquilizers

When using this product

- avoid alcoholic beverages

Stop use and ask a doctor if

sleeplessness persists continuously for more than 2 weeks. Insomnia may be a symptom of serious underlying medical illness.

If pregnant or breast-feeding,

ask a health professional before use.

Keep out of reach of children.

In case of overdose, get medical help or contact a Poison Control Center right away (1-800-222-1222).

Directions

- take only one dose per day (24 hours)
- only use the dose cup provided

adults & children 12 yrs & over | 30 mL at bed time if needed or as directed by a doctor
children under 12 yrs | do not use

Other information

- each 30 mL contains: sodium 20 mg
- store at 20-25°C (68-77°F)

Inactive ingredients

alcohol, anhydrous citric acid, FD&C blue #1, FD&C red #40, flavor, high fructose corn syrup, poloxamer 407, propylene glycol, purified water, saccharin sodium, sodium benzoate, sodium citrate

Questions or comments?

1-888-423-0139

Package/Label Principal Display Panel

TopCare® health

NIGHTTIME

COMPARE TO VICKS® ZZZQUIL® ACTIVE INGREDIENT

ZZZ Sleep®

DIPHENHYDRAMINE HCl 50 mg per 30 mL

NIGHTTIME SLEEP-AID

• Non-Habit Forming

• Not for Treating Cold or Flu

ALCOHOL 10%

6 FL OZ (177 mL)

BERRY FLAVOR